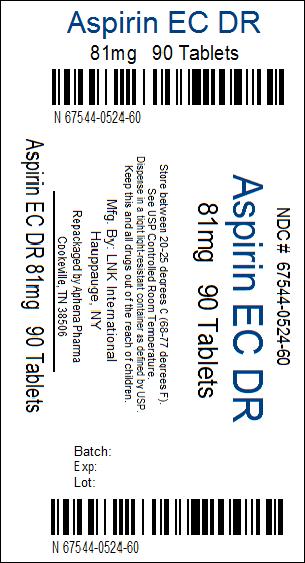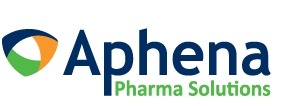 DRUG LABEL: Aspirin EC
NDC: 67544-524 | Form: TABLET, COATED
Manufacturer: Aphena Pharma Solutions - Tennessee, LLC
Category: otc | Type: HUMAN OTC DRUG LABEL
Date: 20130605

ACTIVE INGREDIENTS: ASPIRIN 81 mg/1 1
INACTIVE INGREDIENTS: ANHYDROUS LACTOSE; CARNAUBA WAX; SILICON DIOXIDE; CROSCARMELLOSE SODIUM; D&C YELLOW NO. 10; ALUMINUM OXIDE; FERRIC OXIDE YELLOW; METHACRYLIC ACID - ETHYL ACRYLATE COPOLYMER (1:1) TYPE A; CELLULOSE, MICROCRYSTALLINE; POLYSORBATE 80; SODIUM HYDROXIDE; SODIUM LAURYL SULFATE; TALC; TITANIUM DIOXIDE; TRIETHYL CITRATE

Aspirin EC Tablets, 81 mg

Drug Facts

Active ingredient (in each tablet)

Aspirin 81 mg (NSAID [nonsteroidal anti-inflammatory drug])

Purpose

Pain reliever

Uses

- temporarily relieves minor aches and pains
- for other uses, see your doctor, but do not use for more than 10 days without consulting your doctor because serious side effects may occur

Warnings

Reye's syndrome

Children and teenagers who have or are recovering from chicken pox or flu-like symptoms should not use this product. When using this product, if changes in behavior with nausea and vomiting occur, consult a doctor because these symptoms could be an early sign of Reye's syndrome, a rare but serious illness.

Allergy alert

Aspirin may cause a severe allergic reaction, which may include:

- hives
- facial swelling
- shock
- asthma (wheezing)

Stomach bleeding warning

This product contains an NSAID, which may cause severe stomach bleeding. The chance is higher if you:

- are age 60 or older
- have had stomach ulcers or bleeding problems
- take a blood thinning (anticoagulant) or steroid drug
- take other drugs containing prescription or nonprescription NSAIDs (aspirin, ibuprofen, naproxen, or others)
- have 3 or more alcoholic drinks every day while using this product
- take more or for a longer time than directed

Do not use

- if you are allergic to aspirin or any other pain reliever/fever reducer

Ask a doctor before use if

- stomach bleeding warning applies to you
- you have a history of stomach problems, such as heartburn
- you have high blood pressure, heart disease, liver cirrhosis, or kidney disease
- you are taking a diuretic
- you have asthma
- you have not been drinking fluids
- you have lost a lot of fluid due to vomiting or diarrhea

Ask a doctor or pharmacist before use if you are

- taking a prescription drug for diabetes, gout, or arthritis
- taking any other drug
- under a doctor's care for any serious condition

Stop use and ask a doctor if

- you experience any of the following signs of stomach bleeding:
  - feel faint
  - have bloody or black stools
  - vomit blood
  - have stomach pain that does not get better
- pain gets worse or lasts more than 10 days
- fever gets worse or lasts more than 3 days
- redness or swelling is present in the painful area
- any new symptoms appear
- ringing in the ears or a loss of hearing occurs

PREGNANCY OR BREAST FEEDING

If pregnant or breast-feeding, ask a health professional before use. It is especially important not to use aspirin during the last 3 months of pregnancy unless definitely directed to do so by a doctor because it may cause problems in the unborn child or complications during delivery.

Keep out of reach of children. In case of overdose, get medical help or contact a Poison Control Center right away.

Directions

- drink a full glass of water with each dose
- adults and children 12 years and over: take 4 to 8 tablets every 4 hours not to exceed 48 tablets in 24 hours unless directed by a doctor
- children under 12 years: consult a doctor

Other information

- store at 25°C (77°F) excursions permitted between 15°-30°C (59°-86°F)
- use by expiration date on package

Inactive ingredients

anhydrous lactose, carnauba wax, colloidal silicon dioxide, croscarmellose sodium, D&C yellow #10 aluminum lake, iron oxide ochre, methacrylic acid copolymer, microcrystalline cellulose, polysorbate 80, simethicone, sodium hydroxide, sodium lauryl sulfate, talc, titanium dioxide, triethyl citrate

Questions?

call 1-888-838-2872, weekdays, 8 AM-5 PM ET

Repackaged by Aphena Pharma Solutions - TN.
See Repackaging Information for available configurations.

Distributed by: GOLDLINE LABORATORIES, INC., Sellersville, PA 18960

Dist. 1993 0711REV 89 387R

TAMPER-EVIDENT: DO NOT USE THIS PRODUCT IF THE IMPRINTED FOIL SEAL OVER THE MOUTH OF THE BOTTLE IS CUT, TORN, BROKEN OR MISSING

** This product is not manufactured or distributed by Bayer HealthCare LLC, owner of the registered trademark Bayer® Low Dose.

Repackaging Information

Please reference the Product Characteristics section listed below for a description of individual tablets or capsules. This drug product has been received by Aphena Pharma - TN in a manufacturer or distributor packaged configuration and repackaged in full compliance with all applicable cGMP regulations. The package configurations available from Aphena are listed below:

Count | 81mg
30 | 67544-524-30
90 | 67544-524-60

Store between 20°-25°C (68°-77°F). See USP Controlled Room Temperature. Dispense in a tight light-resistant container as defined by USP. Keep this and all drugs out of the reach of children.

Repackaged by:
Cookeville, TN 38506
20130605AW

PRINCIPAL DISPLAY PANEL - 81mg

NDC 67544-524 - Aspirin 81mg